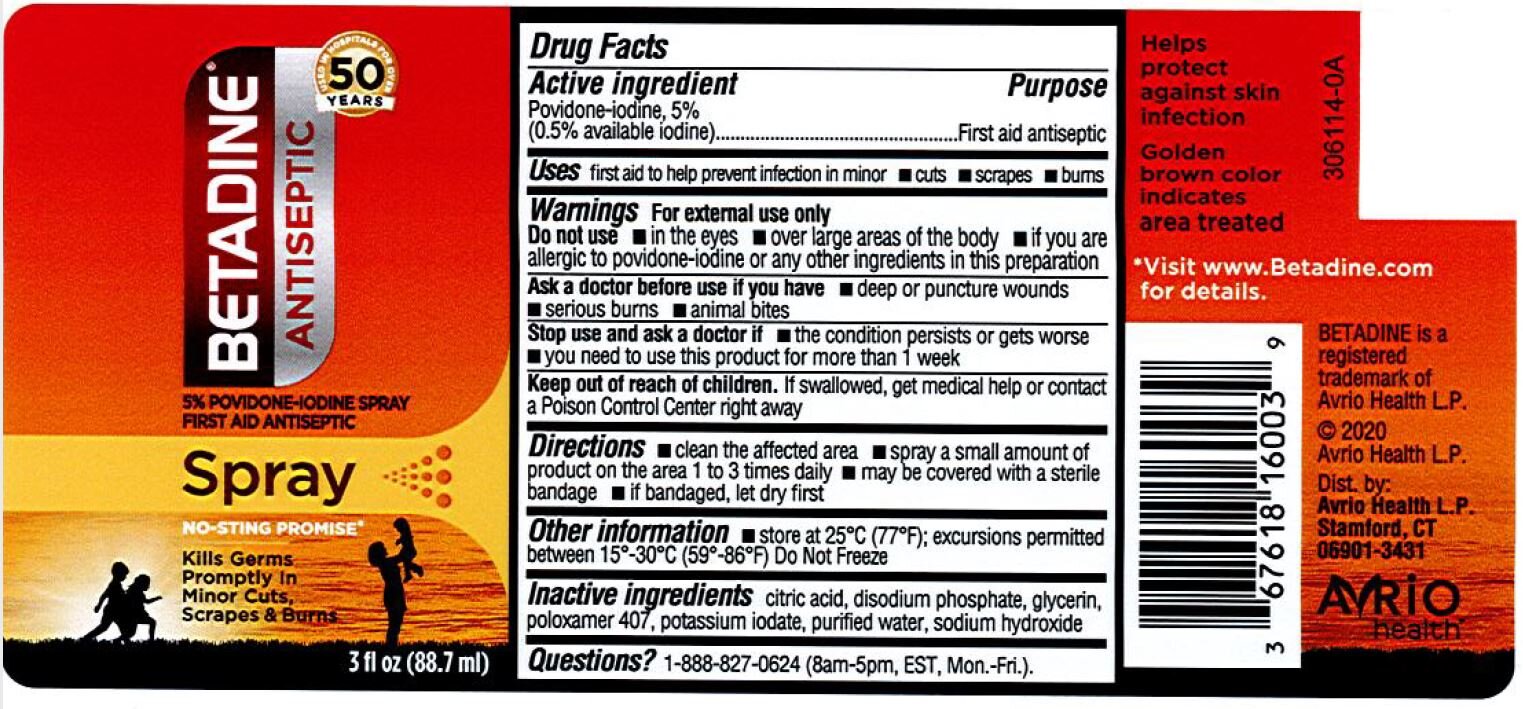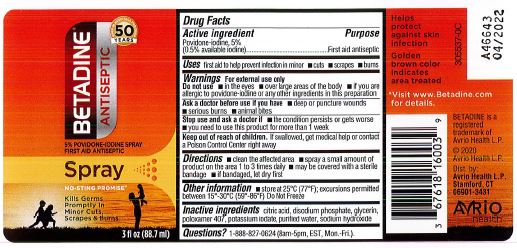 DRUG LABEL: Povidone Iodine
NDC: 0395-9129 | Form: LIQUID
Manufacturer: Humco Holding Group, Inc.
Category: otc | Type: HUMAN OTC DRUG LABEL
Date: 20231215

ACTIVE INGREDIENTS: POVIDONE-IODINE 50 mg/1 mL
INACTIVE INGREDIENTS: POTASSIUM IODATE; CITRIC ACID MONOHYDRATE; SODIUM PHOSPHATE, DIBASIC; GLYCERIN; WATER; POLOXAMER 407; SODIUM HYDROXIDE

Private Label Povidone Iodine Spray 5%

Active Ingredient

Povidone-Iodine 5%

(0.5% available iodine)

Warnings

For external use only.

Do not use:

- In the eyes
- Over large areas of the body
- If you are allergic to povidone-iodine or any other ingredients in this preparation

Ask a doctor before use if you have:

- Deep or puncture wounds
- Serious burns
- Animal bites

Stop and ask a doctor if:

- The condition persists or gets worse
- You need to use this product for more that 1 week

Keep out of reach of children

If swallowed, get medical help or contact a Poison Control Center right away.

Other Information

Store at 25°C (77°F); Excursions permitted between 15-30°C (59-86°F). Do not freeze.

Inactive ingredients:

citric acid, disodium phosphate, glycerin, poloxamer 407, potassium iodata, purified water, sodium hydroxide.

Directions:

- Clean the affected area
- Spray a small amount of product on the area 1 to 3 times daily
- May be covered with a sterile bandage
- If bandaged, let dry first

Uses

First aid to help prevent infection in minor

- cuts
- scrapes
- burns

Purpose

Antiseptic

Drug Facts